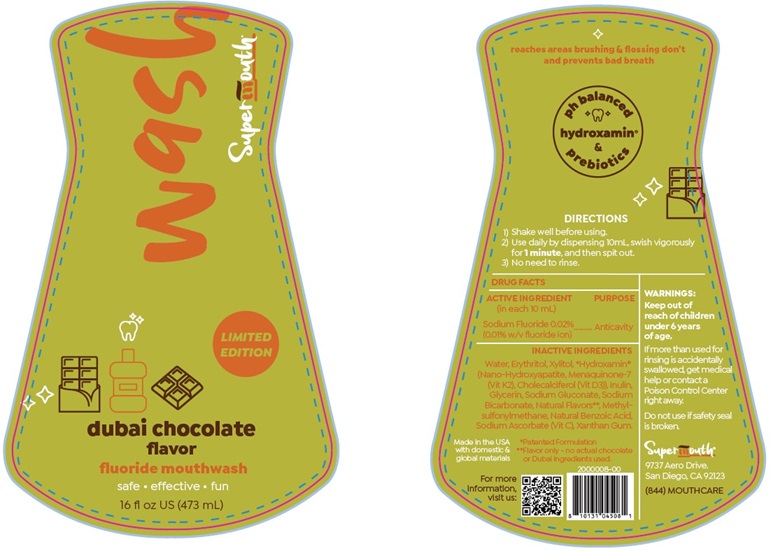 DRUG LABEL: Dubai Chocolate Fluoride Mouthwash
NDC: 83729-120 | Form: LIQUID
Manufacturer: SuperMouth, LLC.
Category: otc | Type: HUMAN OTC DRUG LABEL
Date: 20250723

ACTIVE INGREDIENTS: SODIUM FLUORIDE 0.002 mg/10 mL
INACTIVE INGREDIENTS: WATER; ERYTHRITOL; XYLITOL; TRIBASIC CALCIUM PHOSPHATE; MENAQUINONE 7; CHOLECALCIFEROL; INULIN; GLYCERIN; SODIUM GLUCONATE; SODIUM BICARBONATE; DIMETHYL SULFONE; BENZOIC ACID; SODIUM ASCORBATE; XANTHAN GUM

Dubai Chocolate Flavor Fluoride Mouthwash

ACTIVE INGREDIENT
(in each 10 mL)

Sodium Fluoride 0.02%

PURPOSE
Sodium Fluoride …. Anticavity

USE

Fluoride mouthwash

WARNINGS:

Keep out of reach of children under 6 years of age.

OTHER SAFETY INFORMATION

If more than used for
rinsing is accidentally
swallowed, get medical
help or contact a
Poison Control Center
right away.

Do not use if safety seal
is broken.

DIRECTIONS

1) Shake well before using.
2) Use daily by dispensing 10 mL, swish
vigorously for 1 minute, and then spit out.
3) No need to rinse.

INACTIVE INGREDIENTS

Water, Erythritol, Xylitol, *Hydroxamin®
(Nano-Hydroxyapatite, Menaquinone-7
(Vit K2), Cholecalciferol (Vit D3)), Inulin,
Glycerin, Sodium Gluconate, Sodium
Bicarbonate, Natural Flavors**, Methyl-
sulfonylmethane, Natural Benzoic Acid,
Sodium Ascorbate (Vit C), Xanthan Gum.

*Patented Formulation

**Flavor only - no actual chocolate or Dubai ingredients used.

Product Labeling: Dubai Chocolate Fluoride Mouthwash

Supermouth

dubai chocolate

flavor

fluoride mouthwash

safe • effective • fun

16 fl oz (473 mL)

reaches areas brushing & flossing don’t and prevents bad breath

SuperMouth®
9737 Aero Drive
San Diego, CA 92123

(844) MOUTHCARE

res